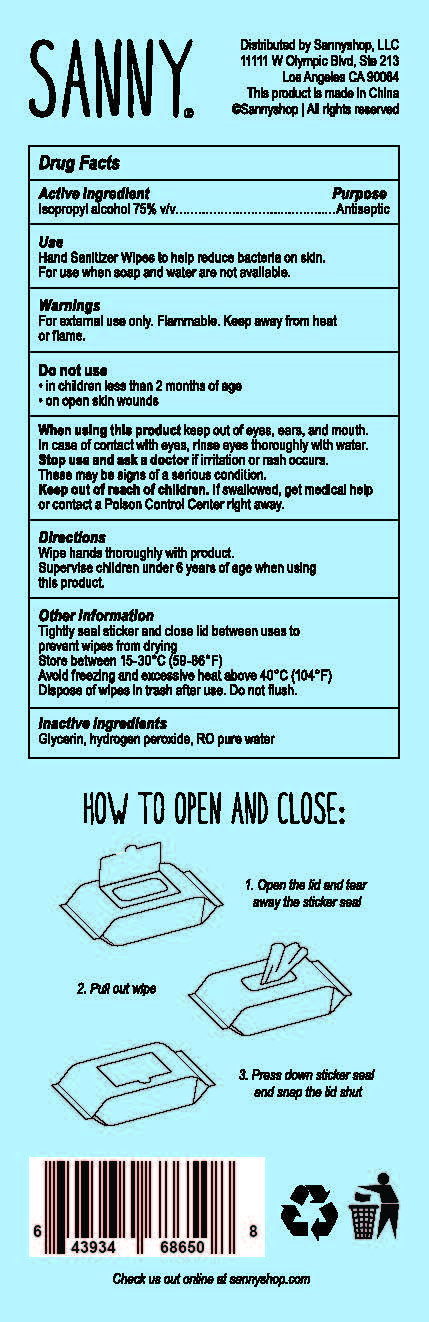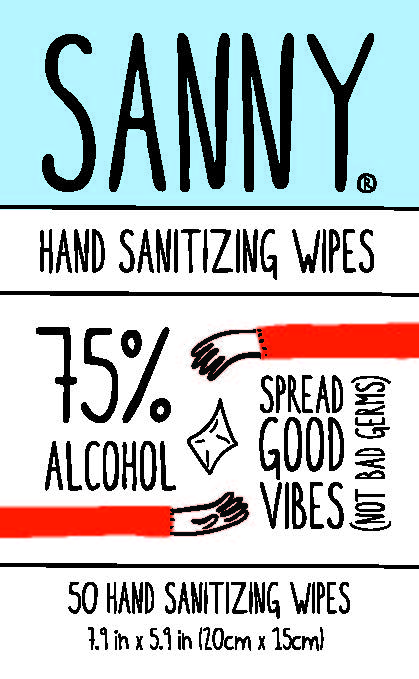 DRUG LABEL: Sanny Hand Sanitizing Wipes
NDC: 78930-111 | Form: CLOTH
Manufacturer: SannyShop LLC
Category: otc | Type: HUMAN OTC DRUG LABEL
Date: 20201124

ACTIVE INGREDIENTS: ISOPROPYL ALCOHOL 75 mL/100 mL
INACTIVE INGREDIENTS: GLYCERIN 1.45 mL/100 mL; HYDROGEN PEROXIDE 0.125 mL/100 mL; WATER

This is a hand sanitizer manufactured according to the Temporary Policy for Preparation of Certain Alcohol-Based Hand Sanitizer Products During the Public Health Emergency (CoViD-19); Guidance for Industry.

The hand sanitizer is manufactured using only the following United States Pharmacopoeia (USP) grade ingredients in the preparation of the product (percentage in final product formulation) consistent with World Health Organization (WHO) recommendations:

1. Isopropyl Alcohol (75%, v/v) in an aqueous solution denatured according to Alcohol and Tobacco Tax and Trade Bureau regulations in 27 CFR part 20.
2. Glycerol (1.45% v/v).
3. Hydrogen peroxide (0.125% v/v).
4. Sterile distilled water or boiled cold water.

The firm does not add other active or inactive ingredients. Different or additional ingredients may impact the quality and potency of the product.

Active Ingredient(s)

Isopropyl Alcohol 75% v/v. Purpose: Antiseptic

Purpose

Antiseptic

Use

Hand Sanitizer to help reduce bacteria on skin. For use when soap and water are not available.

Warnings

For external use only. Flammable. Keep away from heat or flame

Do not use

- in children less than 2 months of age
- on open skin wounds

When using this product keep out of eyes, ears, and mouth. In case of contact with eyes, rinse eyes thoroughly with water.
Stop use and ask a doctor if irritation or rash occurs. These may be signs of a serious condition.
Keep out of reach of children. If swallowed, get medical help or contact a Poison Control Center right away.

Stop use and ask a doctor if irritation or rash occurs. These may be signs of a serious condition.

Keep out of reach of children. If swallowed, get medical help or contact a Poison Control Center right away.

Directions

- Wipe hands thoroughly with product.
- Supervise children under 6 years of age when using this product.

Other information

- Tightly seal sticker and close lid between uses to prevent wipes from drying
- Store between 15-30C (59-86F)
- Avoid freezing and excessive heat above 40C (104F)
- Dispose of wipes in trash after use. Do not flush.

Inactive ingredients

glycerin, hydrogen peroxide, RO pure water

Package Label - Principal Display Panel

SANNY

HAND SANITIZING WIPES

75% ALCOHOL

SPREAD GOOD VIBES NOT BAD GERMS

50 HAND SANITIZING WIPES

7.9 IN X 5.9 IN (20cm X 15 cm)